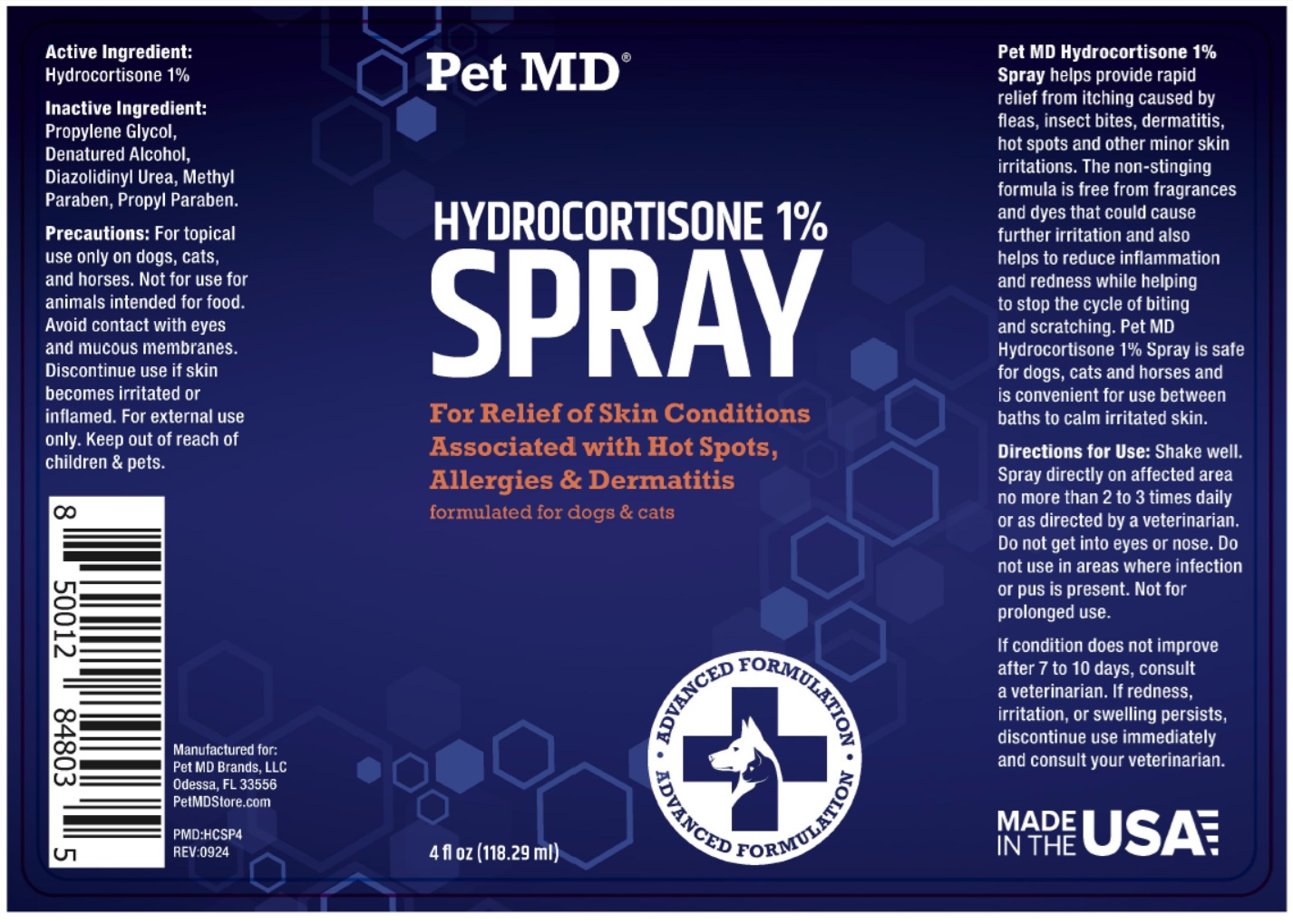 DRUG LABEL: Pet MD HYDROCORTISONE 1%
NDC: 86090-017 | Form: SPRAY
Manufacturer: Pet MD Brands, LLC
Category: animal | Type: OTC ANIMAL DRUG LABEL
Date: 20251112

ACTIVE INGREDIENTS: HYDROCORTISONE 10 mg/1 mL
INACTIVE INGREDIENTS: PROPYLENE GLYCOL; ALCOHOL; DIAZOLIDINYL UREA; METHYLPARABEN; PROPYLPARABEN

Pet MD® HYDROCORTISONE 1% SPRAY

Active Ingredient:

Hydrocortisone 1%

Inactive Ingredient:

Propylene Glycol, Denatured Alcohol, Diazolidinyl Urea, Methyl Paraben, Propyl Paraben.

Precautions:

For topical use only on dogs, cats, and horses. Not for use for animals intended for food. Avoid contact with eyes and mucous membranes. Discontinue use if skin becomes irritated or inflamed. For external use only. Keep out of reach of children & pets.

INDICATIONS AND USAGE

Pet MD Hydrocortisone 1% Spray helps provide rapid relief from itching caused by fleas, insect bites, dermatitis, hot spots and other minor skin irritations. The non-stinging formula is free from fragrances and dyes that could cause further irritation and also helps to reduce inflammation and redness while helping to stop the cycle of biting and scratching. Pet MD Hydrocortisone 1% Spray is safe for dogs, cats and horses and is convenient for use between baths to calm irritated skin.

Directions for Use:

Shake well. Spray directly on affected area no more than 2 to 3 times daily or as directed by a veterinarian. Do not get into eyes or nose. Do not use in areas where infection or pus is present. Not for prolonged use.

WARNINGS

If condition does not improve after 7 to 10 days, consult a veterinarian. If redness, irritation, or swelling persists, discontinue use immediately and consult your veterinarian.

For Relief of Skin Conditions Associated with Hot Spots, Allergies & Dermatitis

formulated for dogs & cats

ADVANCED FORMULATION

MADE IN THE USA

Manufactured for:
Pet MD Brands, LLC
Odessa, FL 33556
PetMDStore.com